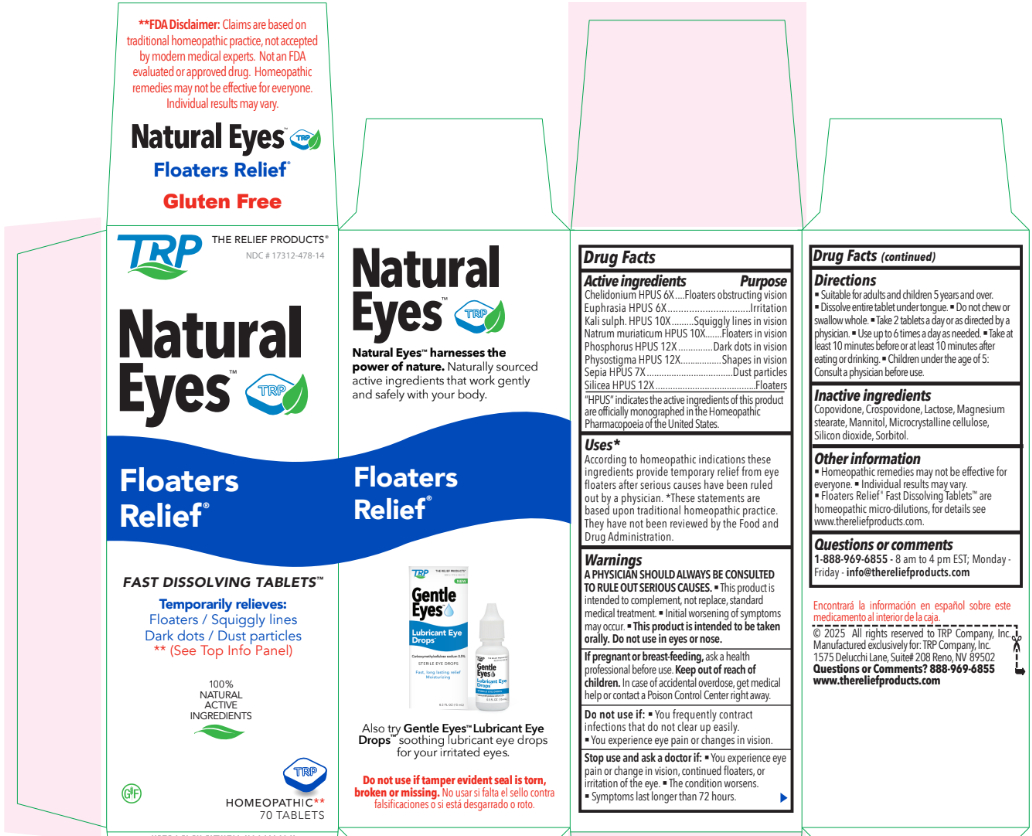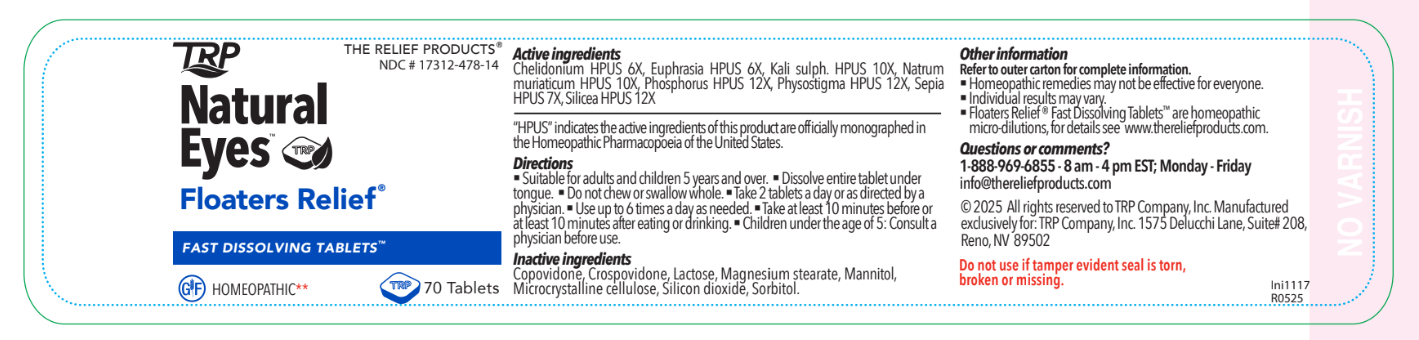 DRUG LABEL: Natural Eyes Floaters Relief
NDC: 17312-478 | Form: TABLET
Manufacturer: TRP Company
Category: homeopathic | Type: HUMAN OTC DRUG LABEL
Date: 20251124

ACTIVE INGREDIENTS: SODIUM CHLORIDE 10 [hp_X]/1 1; POTASSIUM SULFATE 10 [hp_X]/1 1; EUPHRASIA STRICTA 6 [hp_X]/1 1; PHYSOSTIGMA VENENOSUM SEED 12 [hp_X]/1 1; SILICON DIOXIDE 12 [hp_X]/1 1; SEPIA OFFICINALIS JUICE 7 [hp_X]/1 1; CHELIDONIUM MAJUS 6 [hp_X]/1 1; PHOSPHORUS 12 [hp_X]/1 1
INACTIVE INGREDIENTS: COPOVIDONE K25-31; CROSPOVIDONE (120 .MU.M); LACTOSE; MAGNESIUM STEARATE; MANNITOL; MICROCRYSTALLINE CELLULOSE; SORBITOL

Natural Eyes Floaters Relief

Active ingredients

Chelidonium HPUS 6X

Euphrasia HPUS 6X

Kali sulph. HPUS 10X

Natrum muriaticum HPUS 10X

Phosphorus HPUS 12X

Physostigma HPUS 12X

Sepia HPUS 7X

Silicea HPUS 12X

“HPUS” indicates the active ingredients of this product are officially monographed in the Homeopathic Pharmacopoeia of the United States.

Purpose

Chelidonium - Floaters obstructing vision
Euphrasia - Irritation
Kali sulph. - Squiggly lines in vision
Natrum muriaticum - Floaters in vision
Phosphorus - Dark dots in vision
Physostigma - Shapes in vision
Sepia HPUS - Dust particles
Silicea HPUS - Floaters

Uses*
According to homeopathic indications these ingredients provide temporary relief from eye floaters after serious causes have been ruled out by a physician. *These statements are based upon traditional homeopathic practice. They have not been reviewed by the Food and Drug Administration.

Warnings:

A PHYSICIAN SHOULD ALWAYS BE CONSULTEDTO RULE OUT SERIOUS CAUSES.

- This product is intended to complement, not replace, standard medical treatment.
- Initial worsening of symptoms may occur.
- This product is intended to be taken orally. Do not use in eyes or nose.

PREGNANCY OR BREAST FEEDING

If pregnant or breast-feeding, ask a health professional before use.

Do not use if:

- You frequently contract infections that do not clear up easily.
- You experience eye pain or changes in vision.

Keep out of reach of children. In case of accidental overdose, get medical
help or contact a Poison Control Center right away.

Stop use and ask a doctor if:

- You experience eye pain or change in vision, continued floaters, or irritation of the eye.
- The condition worsens.
- Symptoms last longer than 72 hours.

Directions:

- Suitable for adults and children 5 years and over.
- Dissolve entire tablet under tongue.
- Do not chew or swallow whole.
- Take 2 tablets a day or as directed by a physician.
- Use up to 6 times a day as needed.
- Take at least 10 minutes before or at least 10 minutes after eating or drinking.
- Children under the age of 5: Consult a physician before use.

Inactive ingredients
Copovidone, Crospovidone, Lactose, Magnesium stearate, Mannitol, Microcrystalline cellulose, Silicon dioxide, Sorbitol.

Other information:

- Homeopathic remedies may not be effective for everyone.
- Individual results may vary.
- Floaters Relief Fast Dissolving Tablets are homeopathic micro-dilutions, for details see www.thereliefproducts.com.

Questions or Comments

1-888-969-6855 - 8 am to 4 pm EST; Monday - Friday - info@thereliefproducts.com